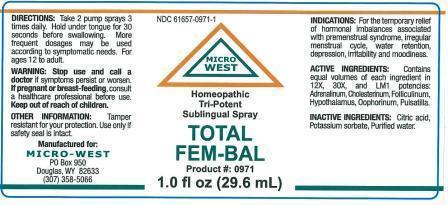 DRUG LABEL: TOTAL FEM-BAL
NDC: 61657-0971 | Form: LIQUID
Manufacturer: WHITE MANUFACTURING INC. DBA MICRO WEST
Category: homeopathic | Type: HUMAN OTC DRUG LABEL
Date: 20140818

ACTIVE INGREDIENTS: EPINEPHRINE 12 [hp_X]/30 mL; PULSATILLA VULGARIS 12 [hp_X]/30 mL; CHOLESTEROL 12 [hp_X]/30 mL; ESTRONE 12 [hp_X]/30 mL; BOS TAURUS HYPOTHALAMUS 12 [hp_X]/30 mL; SUS SCROFA OVARY 12 [hp_X]/30 mL; ANDROSTENEDIONE 30 [hp_X]/30 mL; PRASTERONE 12 [hp_X]/30 mL; PREGNENOLONE 12 [hp_X]/30 mL; PROGESTERONE 12 [hp_X]/30 mL; TESTOSTERONE 12 [hp_X]/30 mL; SUS SCROFA ADRENAL GLAND 12 [hp_X]/30 mL
INACTIVE INGREDIENTS: POTASSIUM SORBATE; CITRIC ACID MONOHYDRATE

DRUG FACTS

ACTIVE INGREDIENTS

EACH MULTI POTENCIES OF 12X, 30X, LM1
ADRENALINUM
CHOLESTERINUM
FOLLICULINUM
HYPOTHALAMUS
OOPHORINUM
PULSATILLA

DIRECTIONS

TAKE 2 PUMP SPRAYS 3 TIMES A DAILY. HOLD UNDER TONGUE FOR 30 SECONDS BEFORE SWALLOWING. MORE FREQUENT DOSAGES MAY BE USED ACCORDING TO SYMPTOMATIC NEEDS. FOR AGES 12 TO ADULT

KEEP OUT OF REACH OF CHILDREN

WARNING

WARNING: WARNINGS: STOP USE AND CALL A DOCTOR if symptoms persist or worsen. CONTAINS ALCOHOL: in case of accidental overdose, consult a poison control center immediately

OTHER INFORMATION: Tamper resistant for your protection. Use only if safety seal is intact

PREGNANCY

IF PREGNANT OR BREAST FEEDING, consult a healthcare professional before use

PURPOSE

FOR HORMONAL IMBALANCES ASSOCIATED WITH PREMENSTRUAL SYNDROME, IRREGULAR MENSTRUAL CYCLE, WATER RETENTION, DEPRESSION, IRRITABILITY AND MOODINESS

INACTIVE INGREDIENTS

POTASSIUM SORBATE, CITRIC ACID, PURIFIED WATER

INDICATIONS

INDICATIONS: FORTHE TEMPORARY RELIEF OF HORMONAL IMBALANCES ASSOCIATED WITH PREMENSTRUAL SYNDROME, IRREGULAR MENSTRUAL CYCLE, WATER RETENTION, DEPRESSION, IRRITABILITY AND MOODINESS

MANUFACTURE

MANUFACTURED FOR

MICRO-WEST

P.O. Box 950

DOUGLAS, WY 82633

1-307-358-5066